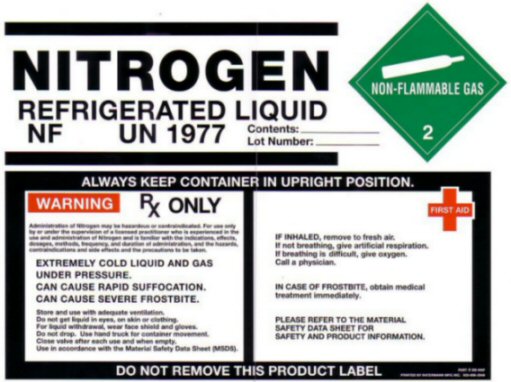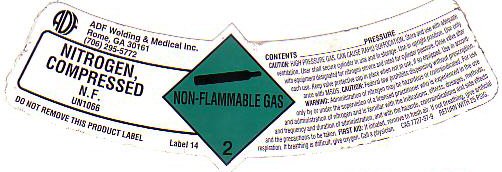 DRUG LABEL: NITROGEN
NDC: 64922-240 | Form: GAS
Manufacturer: ADF Welding & Medical, Inc.
Category: prescription | Type: HUMAN PRESCRIPTION DRUG LABEL
Date: 20241002

ACTIVE INGREDIENTS: NITROGEN 99 L/100 L

Nitrogen

NITROGEN REFRIGERATED LIQUID LABEL

NITROGEN REFRIGERATED LIQUID

NF UN1977 Contents: ________

Lot Number: ______

NON-FLAMMABLE GAS 2

ALWAYS KEEP CONTAINER IN UPRIGHT POSITION.

WARNING Rx ONLY

Administration of Nitrogen may be hazardous or contraindicated. For use only by or under the supervision of a licensed practitioner who is experienced in the use and administration of Nitrogen and is familiar with the indications, effects, dosages, methods, and frequency and duration of administration, and with the hazards, contraindications, and side effects, and the precautions to be taken.

EXTREMELY COLD LIQUI AND GAS UNDER PRESSURE. CAN CAUSE RAPID SUFFOCATION. CAN CAUSE SEVERE FROSTBITE.

Store and use with adequate ventilation. Do not get liquid in eyes, on skin or clothing. For liquid withdrawal, wear face shield and gloves. Do not drop. Use suitable hand truck for container movement. Cylinder temperature should not exceed 52°C (125°F). close valve after each use and when empty. Use a back flow Preventive device in the piping. Use in accordance with the MATERIAL SAFETY DATA SHEET (MSDS).

FIRST AID

IF INHALED, remove to fresh air. If not breathing, give artificial respiration. If breathing is difficult, give oxygen. Call a physician.

IN CASE OF FROSTBITE, obtain medical treatment immediately.

PLEASE REFER TO THE MATERIAL SAFTY DATA SHEET FOR SAFETY AND PRODUCT INFORMATION.

DO NOT REMOVE THIS PRODUCT LABEL

NITROGEN COMPRESSED LABEL

ADF Welding & Medical Inc.

Rome, GA 30161

(706) 295 5772

NITROGEN, COMPRESSED

N.F. UN1066

DO NOT REMOVE THIS PRODUCT LABEL LABEL 14

NON-FLAMMABLE GAS 2

CONTENTS__________________PRESSURE____________

CAUTION: HIGH PRESSURE GAS CAN CAUSE RAPID SUFFOCATION. Store and use with adequate ventilation. User shall secure cylinder in use and in storage. Use in upright position. Use only with equipment designated for Nitrogen service and rated for cylinder pressure. Close valve after each use. Keep valve protective cap in place when not in use if so equipped. Use in accordance with MSDS. CAUTION: Federal law prohibits dispensing without prescription. WARNING: Administrating of Nitrogen may be hazardous or contraindicated. Fore use only by or under the supervision of a licensed practitioner who is experienced in the use and administration of Nitrogen and is familiar with the indications, effects, dosages, methods, and frequency and duration of administration, and with the hazards, contraindications, and side effects and the precautions to be taken. FIRST AID; If inhaled remove to fresh air. If not breathing, give artificial respiration. If breathing is difficult give oxygen, call a physician. CAS 7727-37-9 Return with 25 PSIG